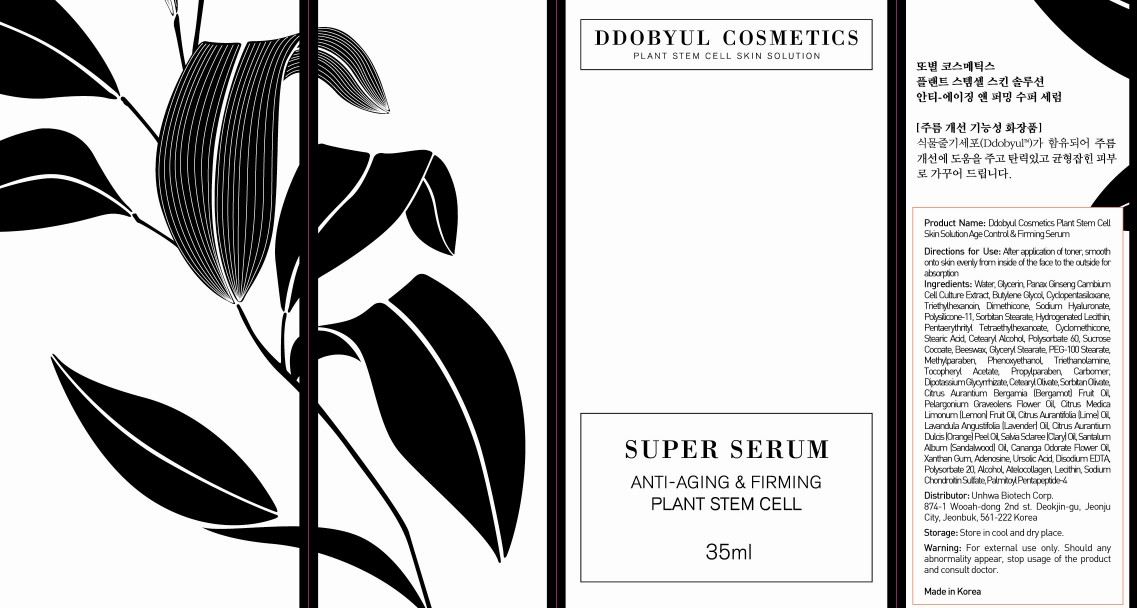 DRUG LABEL: SUPER SERUM
NDC: 50556-003 | Form: CREAM
Manufacturer: UNHWA CORPORATION
Category: otc | Type: HUMAN OTC DRUG LABEL
Date: 20100524

ACTIVE INGREDIENTS: DIMETHICONE 0.7 mL/35 mL

Drug Facts

Active Ingredient: DIMETHICONE

Inactive Ingredients:
Water, Glycerin, Sodium Hyaluronate, Panax Ginseng Cambium Cell Culture Extract, Butylene Glycol, Cyclopentasiloxane, Triethylhexanoin, Polysilicone-11,
Sorbitan Stearate, Hydrogenated Lecithin, Pentaerythrityl Tetraethylhexanoate, Cyclomethicone, Stearic Acid, Cetearyl Alcohol, Polysorbate 60,
Sucrose Cocoate, Beeswax, Glyceryl Stearate, PEG-100 Stearate, Methylparaben, Phenoxyethanol, Triethanolamine, Tocopheryl Acetate, Propylparaben,
Carbomer, Dipotassium Glycyrrhizate, Cetearyl Olivate, Sorbitan Olivate, Fragrance, Xanthan Gum, Adenosine, Ursolic Acid, Disodium EDTA,
Polysorbate 20, Alcohol, Atelocollagen, Lecithin, Sodium Chondroitin Sulfate, Palmitoyl Pentapeptide-4

DESCRIPTION

Directions for Use: After application of toner, smooth onto skin evenly from inside of the face to the outside for absorption.
Storage: Store in cool and dry place.
Warning: For external use only. Should any abnormality appear, stop usage of the product and consult doctor.